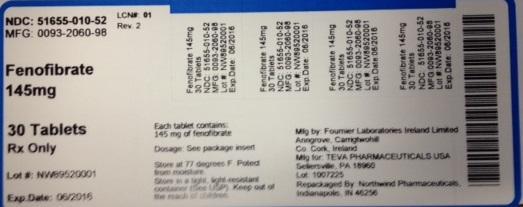 DRUG LABEL: Fenofibrate
NDC: 51655-010 | Form: TABLET
Manufacturer: Northwind Pharmaceuticals
Category: prescription | Type: HUMAN PRESCRIPTION DRUG LABEL
Date: 20140520

ACTIVE INGREDIENTS: FENOFIBRATE 145 mg/30 1

PACKAGE LABEL

NDC: 51655-010-52

MFG: 0093-2060-98

Fenofibrate 145mg

30 Tablets

Rx only

Lot# NW89520001

Exp Date: 06/2016

Each tablet contains: 145mg of fenofibrate

Dosage: See package insert

Store at 77 degrees F. Protect from moisture.

Store in a tight, light-resistant container (See USP) Keep out of reach of children.

Mfg by: Fournier Laboratories Ireland Limited Anngrove, Carrigtwohill Co. Cork, Ireland

Mfg for: Teva Pharmaceuticals USA Sellersville, PA 18960 Lot: 1007225

Repackaged by: Northwind Pharmaceuticals, Indianapolis, IN 46256